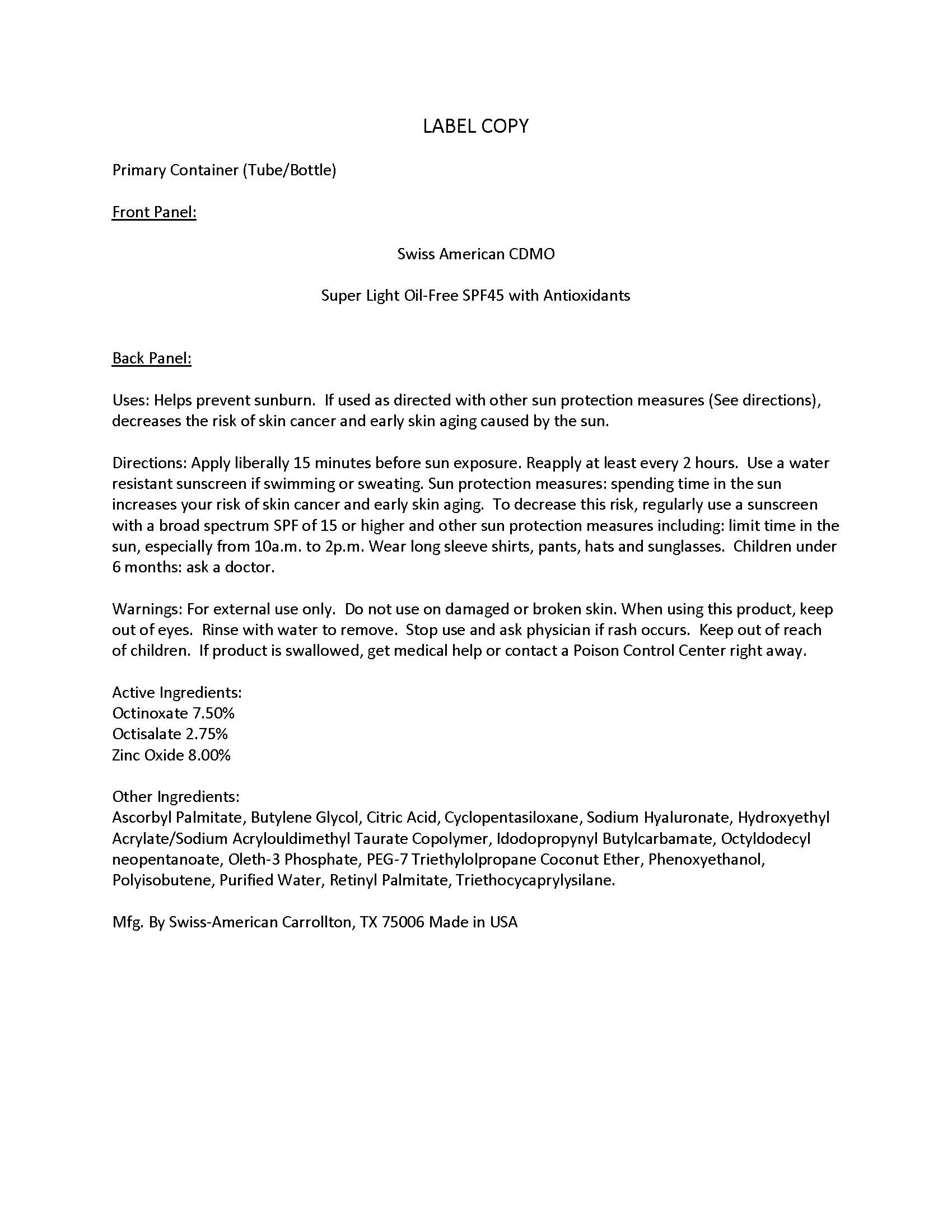 DRUG LABEL: Private Label Super Light Oil-Free SPF45
NDC: 60232-0008 | Form: LOTION
Manufacturer: Swiss-American CDMO, LLC
Category: otc | Type: HUMAN OTC DRUG LABEL
Date: 20231107

ACTIVE INGREDIENTS: OCTISALATE 27.5 g/1000 g; OCTINOXATE 75.0 g/1000 g; ZINC OXIDE 80.0 g/1000 g
INACTIVE INGREDIENTS: WATER; TRIETHOXYCAPRYLYLSILANE; CITRIC ACID MONOHYDRATE; BUTYLENE GLYCOL; PHENOXYETHANOL; IODOPROPYNYL BUTYLCARBAMATE; HYALURONATE SODIUM; CYCLOMETHICONE 5; OCTYLDODECYL NEOPENTANOATE; ASCORBYL PALMITATE; OLETH-3 PHOSPHATE; VITAMIN A PALMITATE; HYDROXYETHYL ACRYLATE/SODIUM ACRYLOYLDIMETHYL TAURATE COPOLYMER (45000 MPA.S AT 1%); POLYISOBUTYLENE (1300 MW)

Private Label Super Light Oil-Free SPF45

Warnings

For external use only. Do not use on damaged or broken skin. When using this product, keep out of eyes. Rinse with water to remove. Stop use and ask physician if rash occurs. Keep out of reach of children. If product is swallowed, get medical help or contact a Poison Control Center right away

Use

Helps prevent sunburn. If used as directed with other sun protection measures (See directions), decreases the risk of skin cancer and early skin aging caused by the sun.

Use

Helps prevent sunburn. If used as directed with other sun protection measures (See directions), decreases the risk of skin cancer and early skin aging caused by the sun.

Directions

Apply liberally 15 minutes before sun exposure. Reapply at least every 2 hours. Use a water resistant sunscreen if swimming or sweating. Sun protection measures: spending time in the sun increases your risk of skin cancer and early skin aging. To decrease this risk, regularly use a sunscreen with a broad spectrum SPF of 15 or higher and other sun protection measures including: limit time in the sun, especially from 10a.m. to 2p.m. Wear long sleeve shirts, pants, hats and sunglasses. Children under 6 months: ask a doctor.

Keep out of reach of children

Active Ingredients

Octinoxate 7.50%

Octisalate 2.75%

Zinc Oxide 8.00%

Inactive Ingredients

Ascorbyl Palmitate, Butylene Glycol, Citric Acid, Cyclopentasiloxane, Sodium Hyaluronate, Hydroxyethyl Acrylate/Sodium Acrylouldimethyl Taurate Copolymer, Idodopropynyl Butylcarbamate, Octyldodecyl neopentanoate, Oleth-3 Phosphate, PEG-7 Triethylolpropane Coconut Ether, Phenoxyethanol, Polyisobutene, Purified Water, Retinyl Palmitate, Triethocycaprylysilane